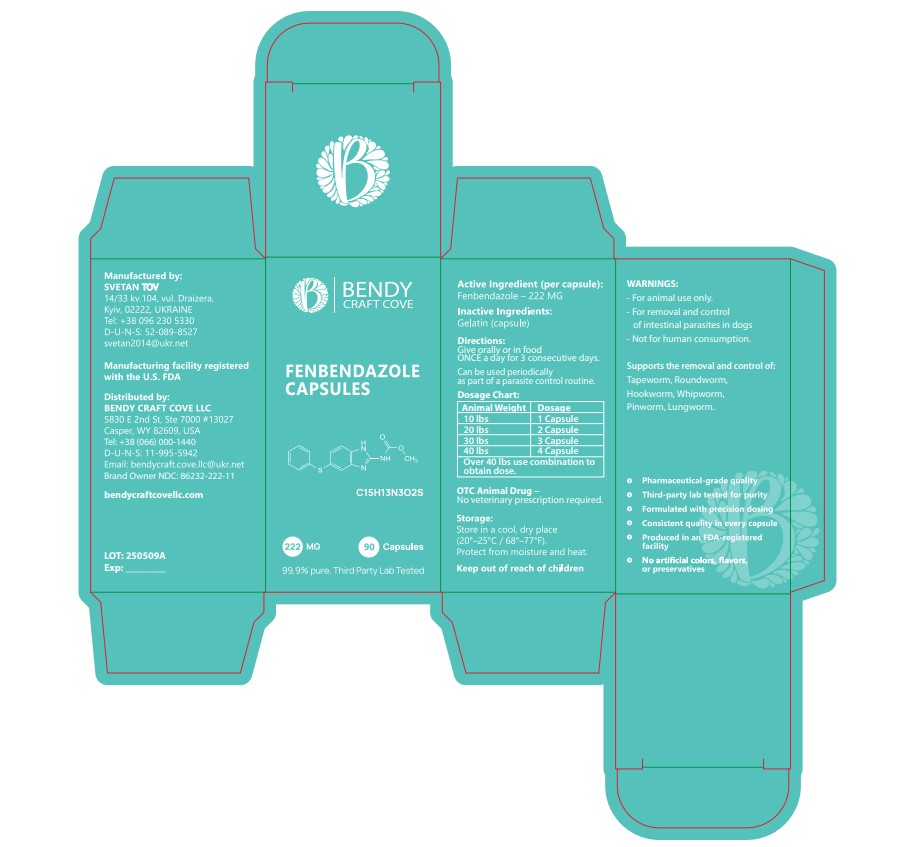 DRUG LABEL: BENDY CRAFT COVE
NDC: 86232-222 | Form: CAPSULE
Manufacturer: BENDYCRAFT COVE LLC
Category: animal | Type: OTC ANIMAL DRUG LABEL
Date: 20250522

ACTIVE INGREDIENTS: FENBENDAZOLE 222 mg/1 U

BENDYCRAFT COVE FENBENDAZOLE

Active Ingredients

Active Ingredients: Fenbendazole 99.99% (222 mg).

Package Labeling

BENDY CRAFT COVE FENBENDAZOLE CAPSULES

C15H13N302S 222MG 90 Capsules 99.9% pure, Third Party Lab Tested

Active Ingredient (per capsule) Fenbendazole - 222 MG Inactive Ingredients: Gelatin (capsule) Directions: Give orally or in food ONCE a day for 3 consecutive days. Can be used periodically as part of a parasite control routine.

Dosage Chart: Dosage Chart: Animal Weight - Dosage 10 lbs - 1 Capsule 20 lbs - 2 Capsule 30 lbs - 3 Capsule 40 lbs - 4 Capsule Over 40lbs use combination to obtain dose. OTC Animal Drug – No veterinary prescription required. Storage: Store in a cool, dry place (20°-25°C / 68°-77°F). Protect from moisture and heat Keep out of reach of children.

WARNINGS: - For animal use only. - For removal and control of intestinal parasites in dogs - Not for human consumption. Supports the removal and control of: Tapeworm, Roundworm, Hookworm, Whipworm, Pinworm, Lungworm. - Pharmaceutical-grade quality - Third-party lab tested for purity - Formulated with precision dosing - Consistent quality in every capsule - Produced in an FDA-registered facility - No artificial colors, flavors, or preservatives.

Manufactured by: SVETAN TOV 14/33 kv.104, vl, Draizera, Kyiv, 02222, UKRAINE Tel: +38 096 230 5330 D-U-N-S: 52-089-8527 svetan2014@ukr.net Manufacturing facility registered with the U.S. FDA

Distributed by: BENDY CRAFT COVE LLC 5830 E 2nd St, Ste 7000 #13027 Casper, WY 82609, USA Tel: +38 (066) 000-1440 D-U-N-S: 11-995-5942 Email: bendycraft.cove.llc@ukr.net bendycraftcovellc.com LOT: 2505090A EXP _____________